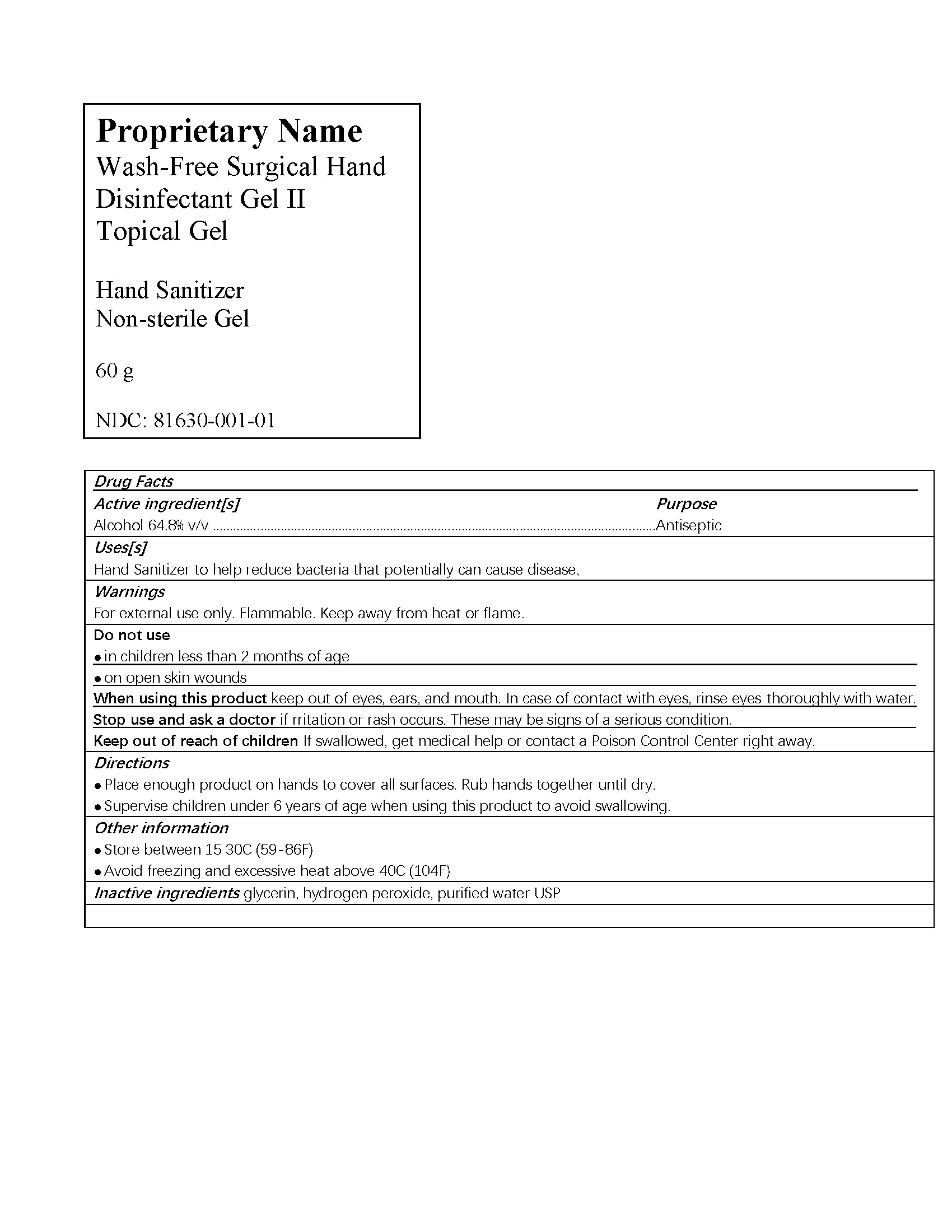 DRUG LABEL: Wash-Free Surgical Hand Disinfectant Gel
NDC: 81630-001 | Form: GEL
Manufacturer: Shan Dong Lircon Medical Technology Co., Ltd
Category: otc | Type: HUMAN OTC DRUG LABEL
Date: 20240808

ACTIVE INGREDIENTS: ALCOHOL 64.8 mL/100 mL
INACTIVE INGREDIENTS: CARBOMER HOMOPOLYMER, UNSPECIFIED TYPE 0.3 mL/100 mL; TROLAMINE 0.1 mL/100 mL; GLYCERIN 2 mL/100 mL; WATER 32.8 mL/100 mL

SPL file for drug listing

Disinfectant type

Antiseptic, Hand Sanitizer

Major ingredient and concentration

This product is a disinfectant gel with ethanol as the main active ingredient, and the ethanol content is 75%±7.5% v/v. Add skin care ingredients such as moisturizers and moisturizers.

Germicidal spectrum

Antiseptic, Hand Sanitizer. It can kill the microorganisms such as enter ic pathogenic bacteria, pyogenic coccus, pathogenic yeast and hospital infect ion common germs.

Application soope

1. Sanitary hand disinfeotion: suitable for hand disinfeotion of medical staff in out patient。linios, wards, emergency room. intensive care units，hemodialysis rooms, and endoscopy rooms of medical and health institutions. It is suitable for quick
disinfeotion of hands of persons who need to perform hand hygiene.

2. Surgical hand disinfection: suitable for preoperative surgical hand disinfection in the operating room of medical and health inst itutions.

Cautions

For external use only. Flammable. Keep away from heat or flame

Do not use

- in children less than 2 months of age
- on open skin wounds

When using this product keep out of eyes, ears, and mouth. In case of contact with eyes, rinse eyes thoroughly with water.
Stop use and ask a doctor if irritation or rash occurs. These may be signs of a serious condition.
Keep out of reach of children. If swallowed, get medical help or contact a Poison Control Center right away.

Stop use and ask a doctor if irritation or rash occurs. These may be signs of a serious condition.

Keep out of reach of children. If swallowed, get medical help or contact a Poison Control Center right away.

Usage

Sanitary hand disinfection: Take an appropriate amount of disinfectant gel (2-3ml) on the palm, rub your hands together to make it evenly spread on each part (ensure that the liquid covers the entire surface), Follow the WS/T313 "Specification of hand hygiene for health care workers
" Appendix A, the method of hand washing for medical workers, rub and disinfect for 1 minute.

Surgical hand disinfection：1. Wash hands and forearms, rinse thoroughly and dry. 2. Take an appropriate amount of disinfectant gel (5-10ml), follow the WS/T313 "Specification of hand hygiene for health care workers " Appendix C Surgical no-wash disinfection method, rub your hands and forearms to the lower third of the upper arms for 3 minutes.Wear sterile gloves after drying.

Other information

Store between 15-30C (59-86F)
Avoid freezing and excessive heat above 40C (104F)

Inactive ingredients

carbomer, triethanolamine, glycerol, purified water.

package

package label is attached